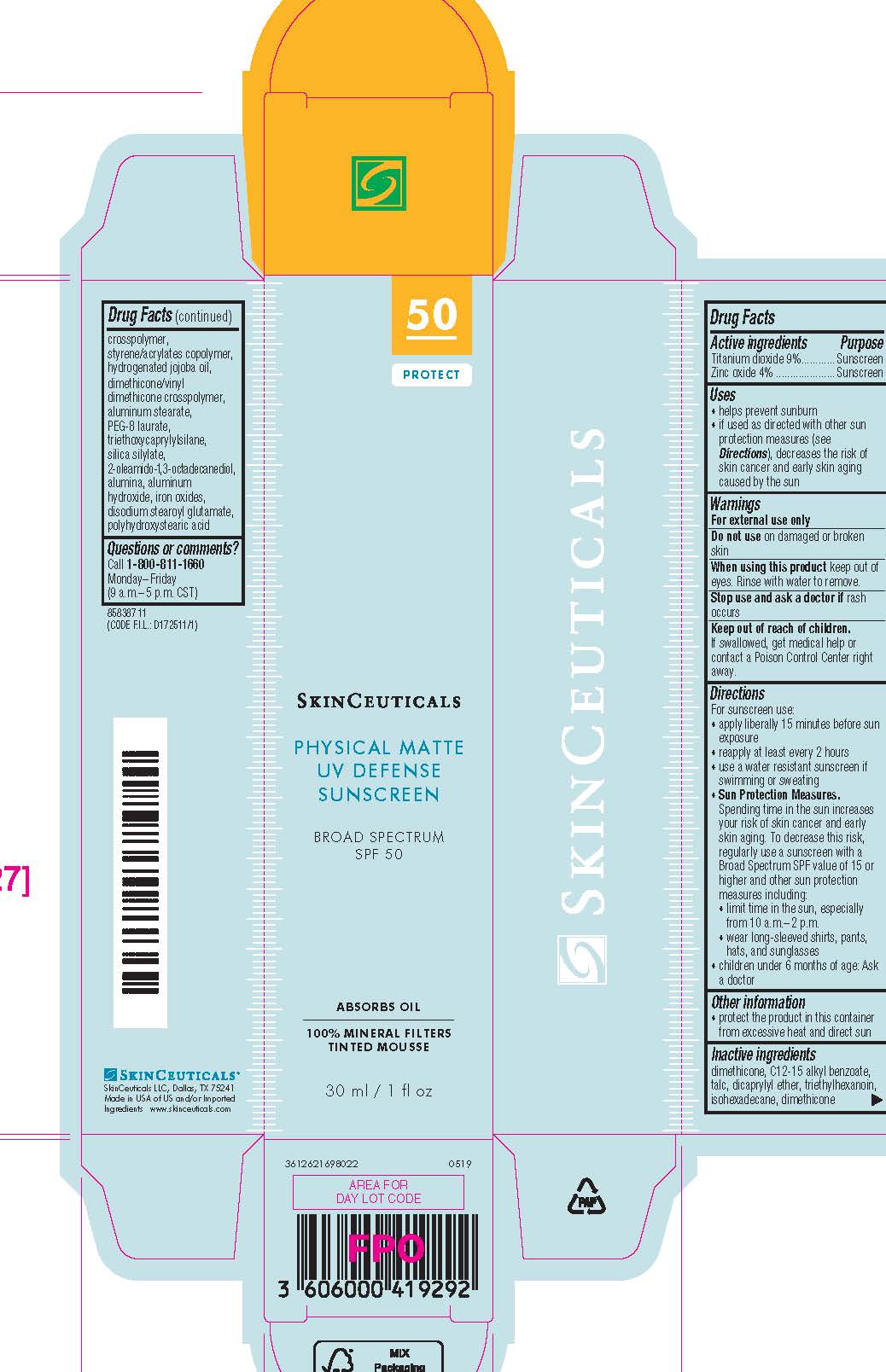 DRUG LABEL: SkinCeuticals Physical Matte UV Defense Broad Spectrum SPF 50 Sunscreen
NDC: 49967-929 | Form: LOTION
Manufacturer: L'Oreal USA Products Inc
Category: otc | Type: HUMAN OTC DRUG LABEL
Date: 20241230

ACTIVE INGREDIENTS: TITANIUM DIOXIDE 90 mg/1 mL; ZINC OXIDE 40 mg/1 mL
INACTIVE INGREDIENTS: DIMETHICONE; ALKYL (C12-15) BENZOATE; TALC; DICAPRYLYL ETHER; TRIETHYLHEXANOIN; ISOHEXADECANE; DIMETHICONE CROSSPOLYMER (450000 MPA.S AT 12% IN CYCLOPENTASILOXANE); STYRENE/ACRYLAMIDE COPOLYMER (500000 MW); HYDROGENATED JOJOBA OIL; DIMETHICONE/VINYL DIMETHICONE CROSSPOLYMER (HARD PARTICLE); ALUMINUM STEARATE; PEG-8 LAURATE; TRIETHOXYCAPRYLYLSILANE; 2-OLEAMIDO-1,3,4-OCTADECATRIYL PROLINATE; ALUMINUM OXIDE; ALUMINUM HYDROXIDE; FERRIC OXIDE RED; DISODIUM STEAROYL GLUTAMATE; POLYHYDROXYSTEARIC ACID (2300 MW)

Drug Facts

Active ingredients

Titanium dioxide 9%

Zinc oxide 4%

Purpose

Sunscreen

Uses

- helps prevent sunburn

- if used as directed with other sun protection measures (see Directions), decreases the risk of skin cancer and early skin aging caused by the sun

Warnings

For external use only

Do not use

on damaged or broken skin

When using this product

keep out of eyes. Rinse with water to remove.

Stop use and ask a doctor if

rash occurs

Keep out of reach of children.

If swallowed, get medical help or contact a Poison Control Center right away.

Directions

● apply liberally 15 minutes before sun exposure

● reapply:

● after 80 minutes of swimming or sweating

● immediately after towel drying

● at least every 2 hours

● Sun Protection Measures. Spending time in the sun increases your risk of skin cancer and early skin aging. To decrease this risk, regularly use a sunscreen with a Broad Spectrum SPF value of 15 or higher and other sun protection measures including:

● limit time in the sun, especially from 10 a.m. – 2 p.m.

● wear long-sleeved shirts, pants, hats, and sunglasses

● children under 6 months of age: Ask a doctor

Other information

protect the product in this container from excessive heat and direct sun

Inactive ingredients

dimethicone, C12-15 alkyl benzoate, dicaprylyl ether, dimethicone/vinyl dimethicone crosspolymer, talc, triethylhexanoin, isohexadecane, styrene/acrylates copolymer, hydrogenated jojoba oil, aluminum hydroxide, stearic acid, aluminum stearate, iron oxides, silica silylate, alumina, polyhydroxystearic acid, PEG-8 laureth, tocopherol, water, diethylhexyl syringylidenemalonate, laureth-4, disodium stearoyul glutamate, cassia alata leaf extract, maltodextrin, caprylic/capric triglyceride

Questions or comments?

Call 1-800-811-1660

Monday - Friday (9 a.m. - 5 p.m. CST)